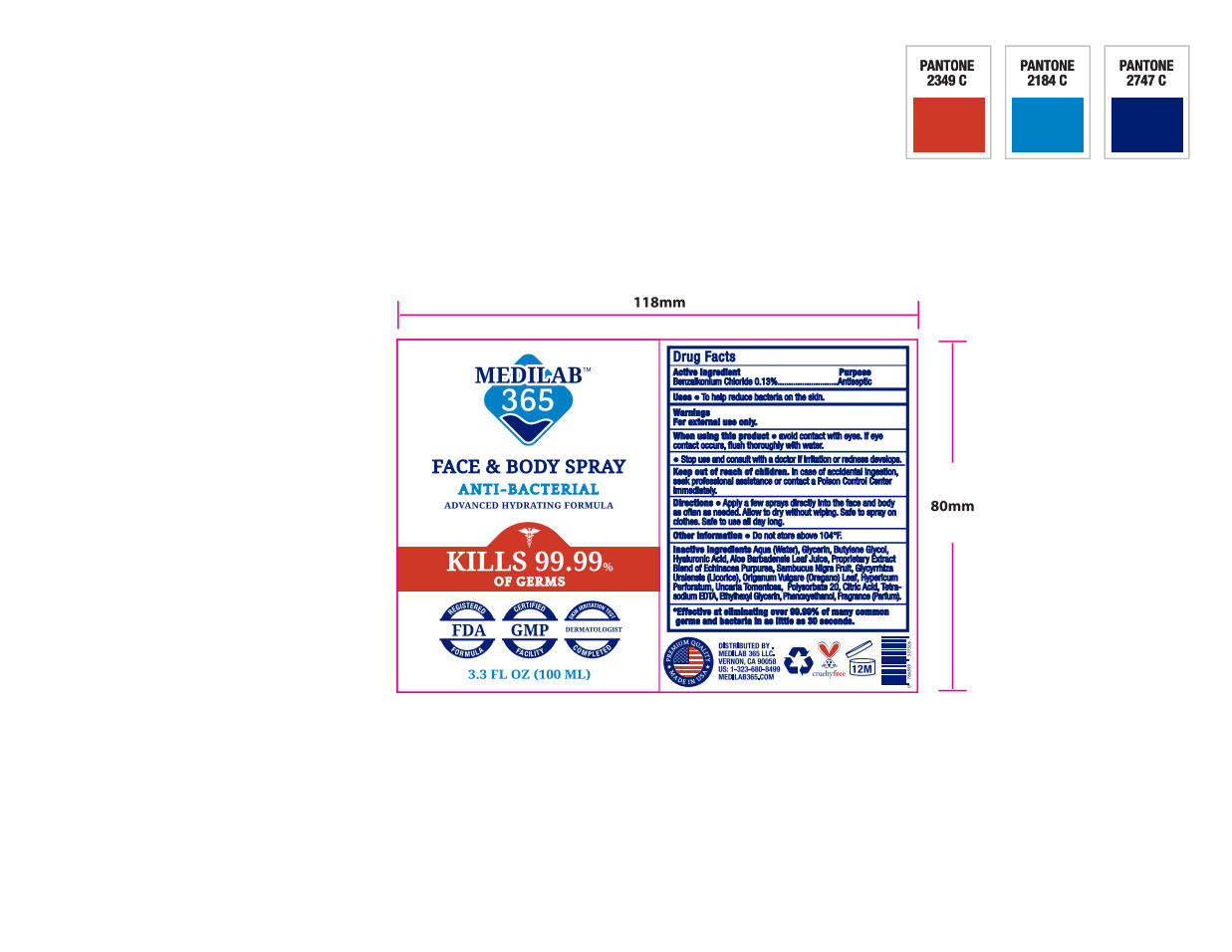 DRUG LABEL: Antimicrobial
NDC: 72471-101 | Form: LIQUID
Manufacturer: VMP Cosmetics
Category: otc | Type: HUMAN OTC DRUG LABEL
Date: 20220122

ACTIVE INGREDIENTS: BENZALKONIUM CHLORIDE 0.13 g/100 g
INACTIVE INGREDIENTS: ETHYLHEXYLGLYCERIN; PHENOXYETHANOL; EUROPEAN ELDERBERRY; UNCARIA TOMENTOSA LEAF; POLYSORBATE 20; CITRIC ACID MONOHYDRATE; EDETATE SODIUM; WATER; ECHINACEA PURPUREA; OREGANO; HYPERICUM PERFORATUM; GLYCERIN; GLYCYRRHIZA URALENSIS; BUTYLENE GLYCOL; HYALURONIC ACID; ALOE VERA LEAF

ACTIVE INGREDIENT

Benzalkonium Chloride 0.13%

PURPOSE SECTION

PURPOSE

Antiseptic

USES

To help reduce bacteria on the skin

WARNINGS

For external use only

When using this product

*avoid contact with eyes. If eye contact occurs, flush thoroughly with water.

Stop use

Stop use and consult with a doctor. If irritation or redness develops.

Keep out of reach of children. In case of accidental ingestion, seek professional assistance or contact a Poison Control Center immediately.

Directions

Directions * Apply a few sprays directly into the face and bodyas often as needed. Allow to dry without wiping. Safe to spray on clothes. Safe to use all day long.

Other Information

Do not store above 104º F.

Inactive Ingredients

Agua (Water),Glycerin, Butylene Glycol, Hyaluronic Acid, Aloe Barbadensis Leaf Juice, Echinacea Purpurea, Sambucus Nigra Fruit, GlycyrrhizaUralensis (Licorice), Origanum Vulgare (Oregano) Leaf, HypericumPerforatum, Uncaria Tomentosa, Polysorbate 20, Citric Acid, Tetrasodium EDTA, Ethylhexylglycerin, Phenoxyethanol, Fragrance.

PDP

MEDILAB

365

FACE & BODY SPRAY

ANTI-BACTERIAL

ADVANCED HYDRATING FORMULA

KILLS 99.99%

OF GERMS

3.3 FL. OZ. (100ML)